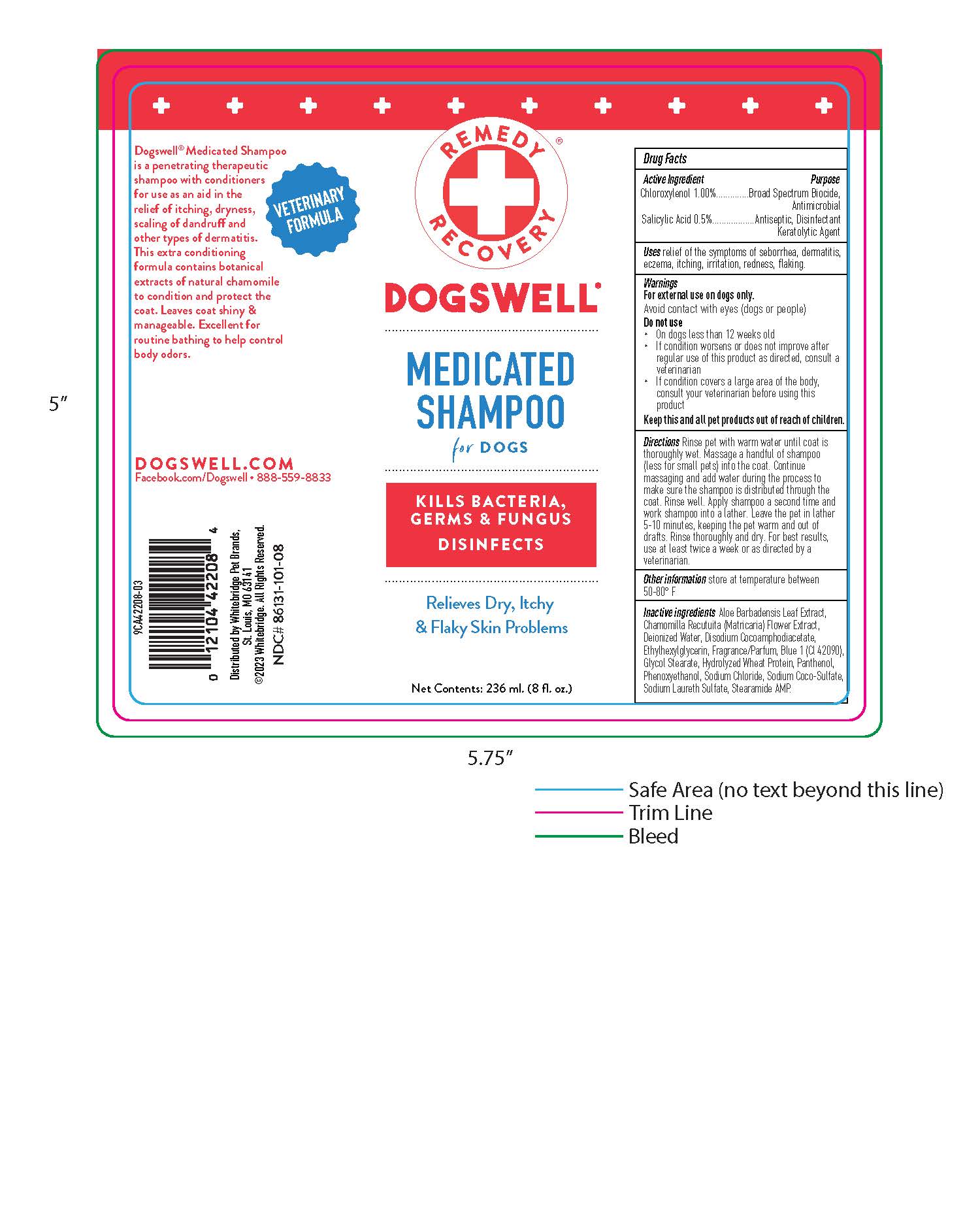 DRUG LABEL: Medicated
NDC: 86131-101 | Form: SHAMPOO
Manufacturer: Whitebridge Pet Brands
Category: animal | Type: OTC ANIMAL DRUG LABEL
Date: 20260123

ACTIVE INGREDIENTS: SALICYLIC ACID 0.5 mg/100 mL; CHLOROXYLENOL 1 mg/100 mL
INACTIVE INGREDIENTS: WATER; ALOE VERA LEAF; PANTHENOL; SODIUM CHLORIDE; SODIUM LAURETH SULFATE; SODIUM COCO-SULFATE; GLYCOL STEARATE; STEARAMIDE AMP; HYDROLYZED WHEAT PROTEIN (ENZYMATIC, 3000 MW); MATRICARIA CHAMOMILLA LEAF; PHENOXYETHANOL; ETHYLHEXYLGLYCERIN

Medicated Shampoo

Other information

store at room temperature between 50-80 F

Drug Facts

Active Ingredients Purpose

Chloroxylenol 1.00% .................... Broad Spectrum Biocide

Controls Mildew

Salicylic Acid 0.5%........................ Antiseptic, Disinfectant

Keratolytic Agent

Warnings

For external use on dogs only.

Avoid contact with eyes (dogs or people)

Do not use

- On dogs less than 12 weeks old
- If condition worsens or does not improve after regular use of this product as directed, consult a veterinarian
- If condition covers a large area of the body, consult your veterinarian before using this product

Keep this an all pet products out of reach of childern.

Uses

relief of the symptoms of seborrhea, dermatitis, eczema, itching, irritation, redness, flaking.

Directions

Rinse pet with warm water until coat is thoroughly wet. Massage a handful of shampoo (less for small pets) into the coat. Continue massaging and add water during the process to make sure the shampoo is distrubuted through the coat. Rinse well. Apply shampoo a second time and work shampoo into lather. Leave the pet in lather 5-10 minutes, keeping the pet warm and out of drafts. Rinse thoroughly and dry. For best results, use at least twice a week or as directed by a veterinarian.

Inactive ingredients

Aloe Barbadensis Leaf Extract, Chamomilla Recutuita (Matricaria) Flower Extract, Deionized Water, Disodium Cocoamphodiacetate, Ethylhexyglycerin, Fragrance/Parfum, Blue 1 (Cl 42090), Glycol Stearate, Hydrolyzed Wheat Protein, Panthenol, Phenoxyethanol, Sodium Chloride, Sodium Coco-Sulfate, Sodium Laureth Sulfate, Stearamide AMP.

Distributed by Whitebridge Pet Brands,

St. Louis, MO 63141

2020 Whitebridge. All Rights Reserved.

NDC# 86131-101-08

PACKAGE LABEL

REMEDY RECOVERY

DOGSWELL

MEDICATED SHAMPOO

for DOGS

KILLS BACTERIA,GERMS & FUNGUS

Relieves Dry, Itchy & Flaky Skin Problems

Net Contents: 236 ml. (8 fl. oz.)